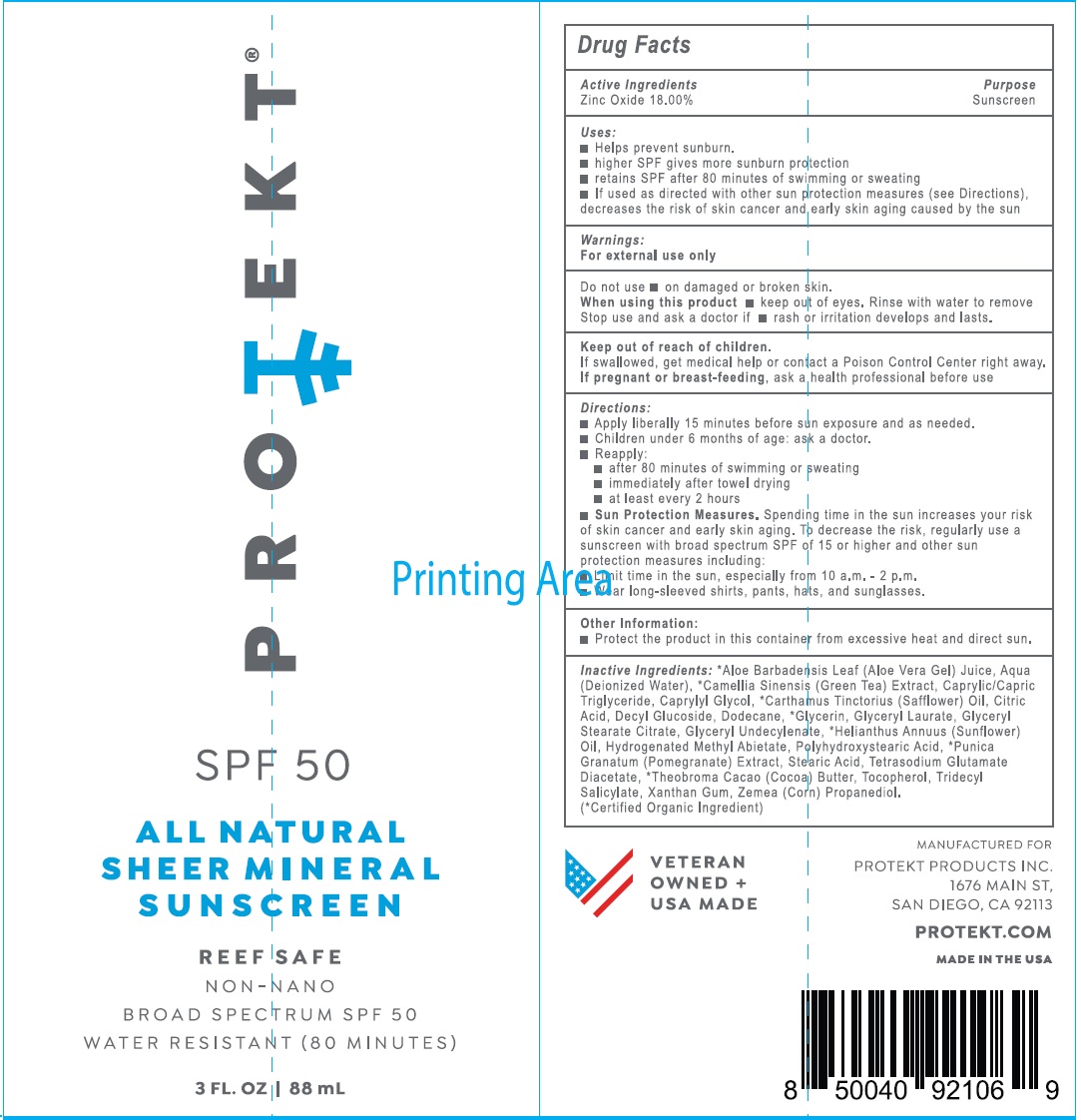 DRUG LABEL: PROTEKT SPF-50 Sheer Mineral Sunscreen
NDC: 82912-322 | Form: CREAM
Manufacturer: Protekt Products, Inc.
Category: otc | Type: HUMAN OTC DRUG LABEL
Date: 20260119

ACTIVE INGREDIENTS: ZINC OXIDE 180 mg/1 mL
INACTIVE INGREDIENTS: ALOE VERA LEAF; WATER; GREEN TEA LEAF; MEDIUM-CHAIN TRIGLYCERIDES; CAPRYLYL GLYCOL; SAFFLOWER; CITRIC ACID MONOHYDRATE; DECYL GLUCOSIDE; DODECANE; GLYCERIN; GLYCERYL LAURATE; GLYCERYL STEARATE CITRATE; HELIANTHUS ANNUUS FLOWERING TOP; HYDROGENATED METHYL ABIETATE; PUNICA GRANATUM ROOT BARK; STEARIC ACID; TETRASODIUM GLUTAMATE DIACETATE; COCOA; TOCOPHEROL; TRIDECYL SALICYLATE; XANTHAN GUM; CORN; PROPANEDIOL

PROTEKT SPF-50 Sheer Mineral Sunscreen

Active Ingredients

Zinc Oxide 18.00%

Purpose

Sunscreen

Uses:

- Helps prevent sunburn.
- higher SPF gives more sunburn protection
- retains SPF after 80 minutes of swimming or sweating
- If used as directed with other sun protection measures (see Directions), decreases the risk of skin cancer and early skin aging caused by the sun

Warnings:

For external use only

Do not use

- on damaged or broken skin.

When using this product

- keep out of eyes. Rinse with water to remove

Stop use and ask a doctor if

- rash or irritation develops and lasts.

Keep out of reach of children.

If swallowed, get medical help or contact a Poison Control Center right away.

If pregnant or breast-feeding,

ask a health professional before use

Directions:

- Apply liberally 15 minutes before sun exposure and as needed.
- Children under 6 months of age: ask a doctor.
- Reapply:
- after 80 minutes of swimming or sweating
- immediately after towel drying
- at least every 2 hours
- Spending time in the sun increases your risk of skin cancer and early skin aging. To decrease the risk, regularly use a sunscreen with broad spectrum SPF of 15 or higher and other sun protection measures including: Sun Protection Measures.
- Limit time in the sun, especially from 10 a.m. - 2 p.m.
- Wear long-sleeved shirts, pants, hats, and sunglasses.

Other Information:

- Protect the product in this container from excessive heat and direct sun.

Inactive Ingredients:

*Aloe Barbadensis Leaf (Aloe Vera Gel) Juice, Aqua (Deionized Water), *Camellia Sinensis (Green Tea) Extract, Caprylic/Capric Triglyceride, Caprylyl Glycol, *Carthamus Tinctorius (Safflower) Oil, Citric Acid, Decyl Glucoside, Dodecane, *Glycerin, Glyceryl Laurate, Glyceryl Stearate Citrate, Glyceryl Undecylenate, *Helianthus Annuus (Sunflower) Oil, Hydrogenated Methyl Abietate, Polyhydroxystearic Acid, *Punica Granatum (Pomegranate) Extract, Stearic Acid, Tetrasodium Glutamate Diacetate, *Theobroma Cacao (Cocoa) Butter, Tocopherol, Tridecyl Salicylate, Xanthan Gum, Zemea (Corn) Propanediol. (*Certified Organic Ingredient)